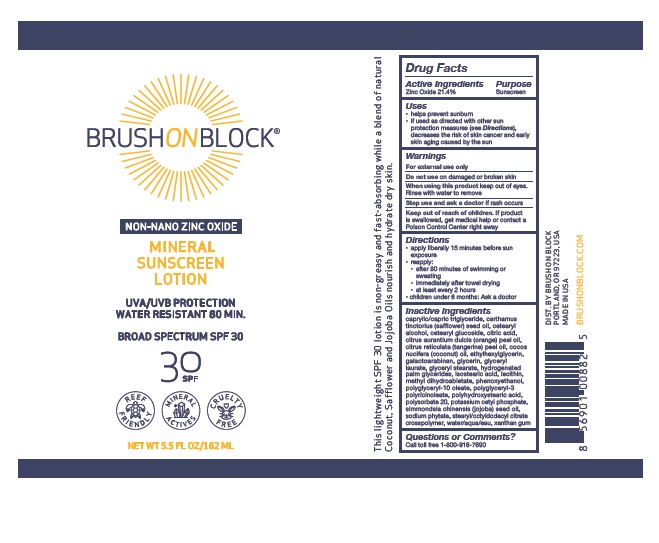 DRUG LABEL: SPF Ventures Brush on Block
NDC: 54111-155 | Form: CREAM
Manufacturer: Bentley Laboratories, LLC
Category: otc | Type: HUMAN OTC DRUG LABEL
Date: 20210516

ACTIVE INGREDIENTS: ZINC OXIDE 21.4 g/100 mL
INACTIVE INGREDIENTS: MEDIUM-CHAIN TRIGLYCERIDES; SAFFLOWER OIL; CETOSTEARYL ALCOHOL; CETEARYL GLUCOSIDE; CITRIC ACID MONOHYDRATE; ORANGE OIL, COLD PRESSED; MANDARIN OIL; COCONUT OIL; ETHYLHEXYLGLYCERIN; GALACTOARABINAN; GLYCERIN; GLYCERYL LAURATE; GLYCERYL MONOSTEARATE; HYDROGENATED PALM GLYCERIDES; ISOSTEARIC ACID; LECITHIN, SUNFLOWER; METHYL DIHYDROABIETATE; PHENOXYETHANOL; POLYGLYCERYL-10 OLEATE; POLYGLYCERYL-3 PENTARICINOLEATE; POLYHYDROXYSTEARIC ACID (2300 MW); POLYSORBATE 20; POTASSIUM CETYL PHOSPHATE; JOJOBA OIL; PHYTATE SODIUM; STEARYL/OCTYLDODECYL CITRATE CROSSPOLYMER; WATER; XANTHAN GUM

SPF Ventures Brush on Block SPF 30

Drug Facts Active ingredients

Zinc Oxide 21.4%

Purpose

Sunscreen

Uses

• helps prevent sunburn
• if used as directed with other sun
protection measures (see Directions),
decreases the risk of skin cancer and early
skin aging caused by the sun

Warnings

For external use only
Do not use on damaged or broken skin
When using this product keep out of eyes.
Rinse with water to remove
Stop use and ask a doctor if rash occurs

Keep out of reach of children.

If swallowed, get medical help or contact a Poison Control Center right away.

Directions

- Apply liberally (generously) 15 minutes before sun exposure
- reapply:

• after 80 minutes of swimming or sweating
• immediately after towel drying
• at least every 2 hours
• Children under 6 months: Ask a doctor

Inactive Ingredients

caprylic/capric triglyceride, carthamus
tinctorius (safflower) seed oil, cetearyl
alcohol, cetearyl glucoside, citric acid,
citrus aurantium dulcis (orange) peel oil,
citrus reticulata (tangerine) peel oil, cocos
nucifera (coconut) oil, ethylhexylglycerin,
galactoarabinan, glycerin, glyceryl
laurate, glyceryl stearate, hydrogenated
palm glycerides, isostearic acid, lecithin,
methyl dihydroabietate, phenoxyethanol,
polyglyceryl-10 oleate, polyglyceryl-3
polyricinoleate, polyhydroxystearic acid,
polysorbate 20, potassium cetyl phosphate,
simmondsia chinensis (jojoba) seed oil,
sodium phytate, stearyl/octyldodecyl citrate
crosspolymer, water/aqua/eau, xanthan gum

Questions or Comments?
Call toll free 1-800-916-7690

BRUSHONBLOCK Labeling

BRUSHONBLOCK®

NON-NANO ZINC OXIDE

MINERAL
SUNSCREEN
LOTION

UVA/UVB PROTECTION
WATER RESISTANT 80 MIN.

BROAD SPECTRUM SPF 30

DIST. BY BRUSH ON BLOCK
PORTLAND, OR 97223, USA
MADE IN USA

BRUSHONBLOCK.COM

RES